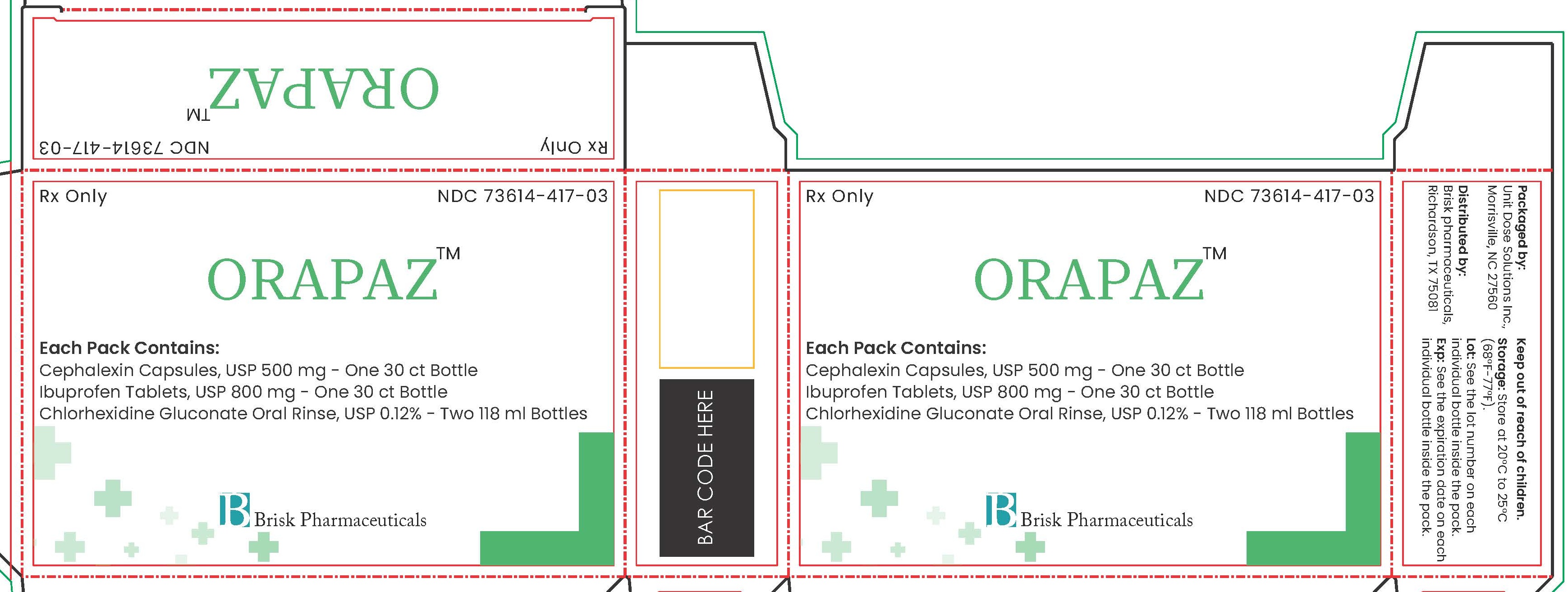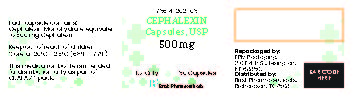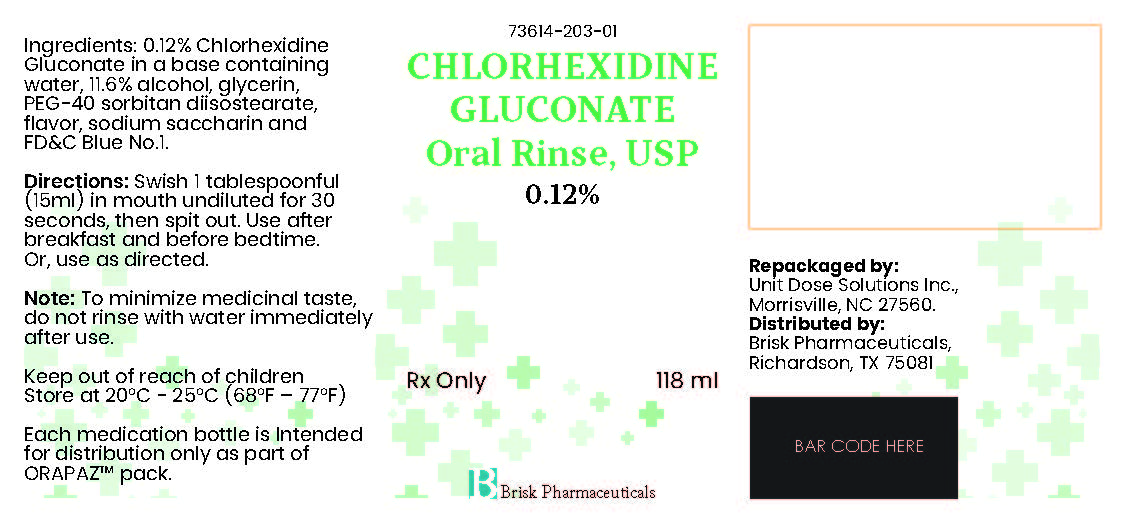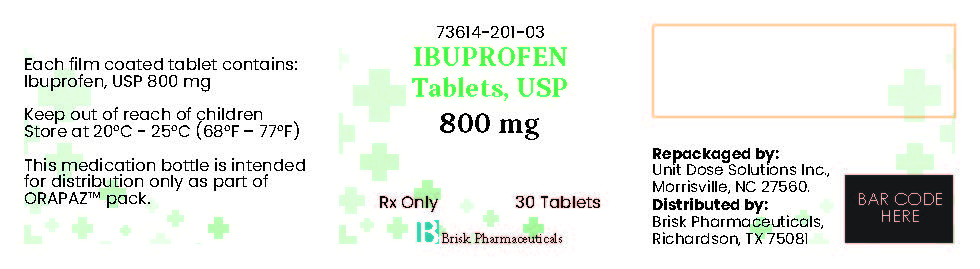 DRUG LABEL: Orapaz
NDC: 73614-417 | Form: KIT | Route: DENTAL
Manufacturer: Brisk Pharmaceuticals
Category: prescription | Type: HUMAN PRESCRIPTION DRUG LABEL
Date: 20250211

ACTIVE INGREDIENTS: CHLORHEXIDINE GLUCONATE 1.2 mg/1 mL; CEPHALEXIN 500 mg/1 1; IBUPROFEN 800 mg/1 1; CHLORHEXIDINE GLUCONATE 1.2 mg/1 mL
INACTIVE INGREDIENTS: ALCOHOL; GLYCERIN; WATER; FD&C BLUE NO. 1; SACCHARIN SODIUM; PEG-40 SORBITAN DIISOSTEARATE; FD&C BLUE NO. 1; TITANIUM DIOXIDE; MICROCRYSTALLINE CELLULOSE; SODIUM LAURYL SULFATE; MAGNESIUM STEARATE; D&C YELLOW NO. 10; GELATIN, UNSPECIFIED; CROSCARMELLOSE SODIUM; FD&C YELLOW NO. 6; CROSCARMELLOSE SODIUM; MAGNESIUM STEARATE; STEARIC ACID; POLYETHYLENE GLYCOL, UNSPECIFIED; SODIUM STARCH GLYCOLATE TYPE A POTATO; SILICON DIOXIDE; MICROCRYSTALLINE CELLULOSE; TITANIUM DIOXIDE; STARCH, CORN; TALC; ALCOHOL; GLYCERIN; WATER; FD&C BLUE NO. 1; SACCHARIN SODIUM; PEG-40 SORBITAN DIISOSTEARATE

Orapaz

DESCRIPTION

Rx Only

NDC 73614-417-03

ORAPAZ™
Each Pack Contains:
Cephalexin Capsules, USP 500 mg - One 30 ct Bottle
Ibuprofen Tablets, USP 800 mg - One 30 ct Bottle
Chlorhexidine Gluconate Oral Rinse, USP 0.12% - Two 118 ml Bottles

Brisk Pharmaceuticals

DESCRIPTION

Packaged by:

Unit Dose Solutions Inc.,

Morrisville, NC 27560

Distributed by:

Brisk pharmaceuticals,

Richardson, TX 75081

Keep out of reach of children.

Storage: Store at 20°C to 25°C

(68°F-77°F).

Lot: See the lot number on each

individual bottle inside the pack.

Exp: See the expiration date on each

individual bottle inside the pack.